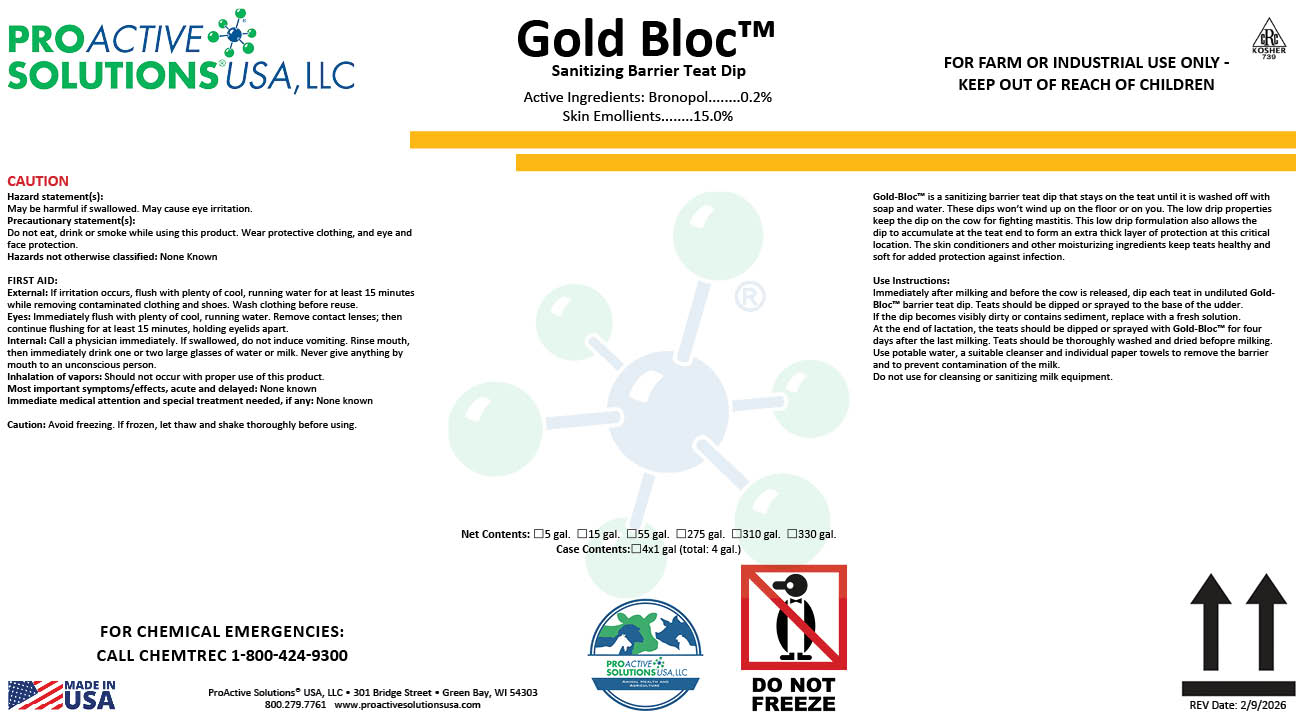 DRUG LABEL: Gold-Bloc
NDC: 63927-4170 | Form: LIQUID
Manufacturer: ProActive Solutions USA, LLC
Category: animal | Type: OTC ANIMAL DRUG LABEL
Date: 20260210

ACTIVE INGREDIENTS: BRONOPOL 0.2 kg/100 kg

Gold-Bloc

Gold-Bloc

Gold-Bloc™ is a sanitizing barrier teat dip that stays on the teat until it is washed off with
soap and water. These dips won’t wind up on the floor or on you. The low drip properties
keep the dip on the cow for fighting mastitis. This low drip formulation also allows the
dip to accumulate at the teat end to form an extra thick layer of protection at this critical
location. The skin conditioners and other moisturizing ingredients keep teats healthy and
soft for added protection against infection.
Use Instructions:
Immediately after milking and before the cow is released, dip each teat in undiluted Gold-
Bloc™ barrier teat dip. Teats should be dipped or sprayed to the base of the udder.
If the dip becomes visibly dirty or contains sediment, replace with a fresh solution.
At the end of lactation, the teats should be dipped or sprayed with Gold-Bloc™ for four
days after the last milking. Teats should be thoroughly washed and dried befopre milking.
Use potable water, a suitable cleanser and individual paper towels to remove the barrier
and to prevent contamination of the milk.
Do not use for cleansing or sanitizing milk equipment.

Hazard statement(s):
May be harmful if swallowed. May cause eye irritation.
Precautionary statement(s):
Do not eat, drink or smoke while using this product. Wear protective clothing, and eye and
face protection.
Hazards not otherwise classified: None Known
FIRST AID:
External: If irritation occurs, flush with plenty of cool, running water for at least 15 minutes
while removing contaminated clothing and shoes. Wash clothing before reuse.
Eyes: Immediately flush with plenty of cool, running water. Remove contact lenses; then
continue flushing for at least 15 minutes, holding eyelids apart.
Internal: Call a physician immediately. If swallowed, do not induce vomiting. Rinse mouth,
then immediately drink one or two large glasses of water or milk. Never give anything by
mouth to an unconscious person.
Inhalation of vapors: Should not occur with proper use of this product.
Most important symptoms/effects, acute and delayed: None known
Immediate medical attention and special treatment needed, if any: None known
Caution: Avoid freezing. If frozen, let thaw and shake thoroughly before using.